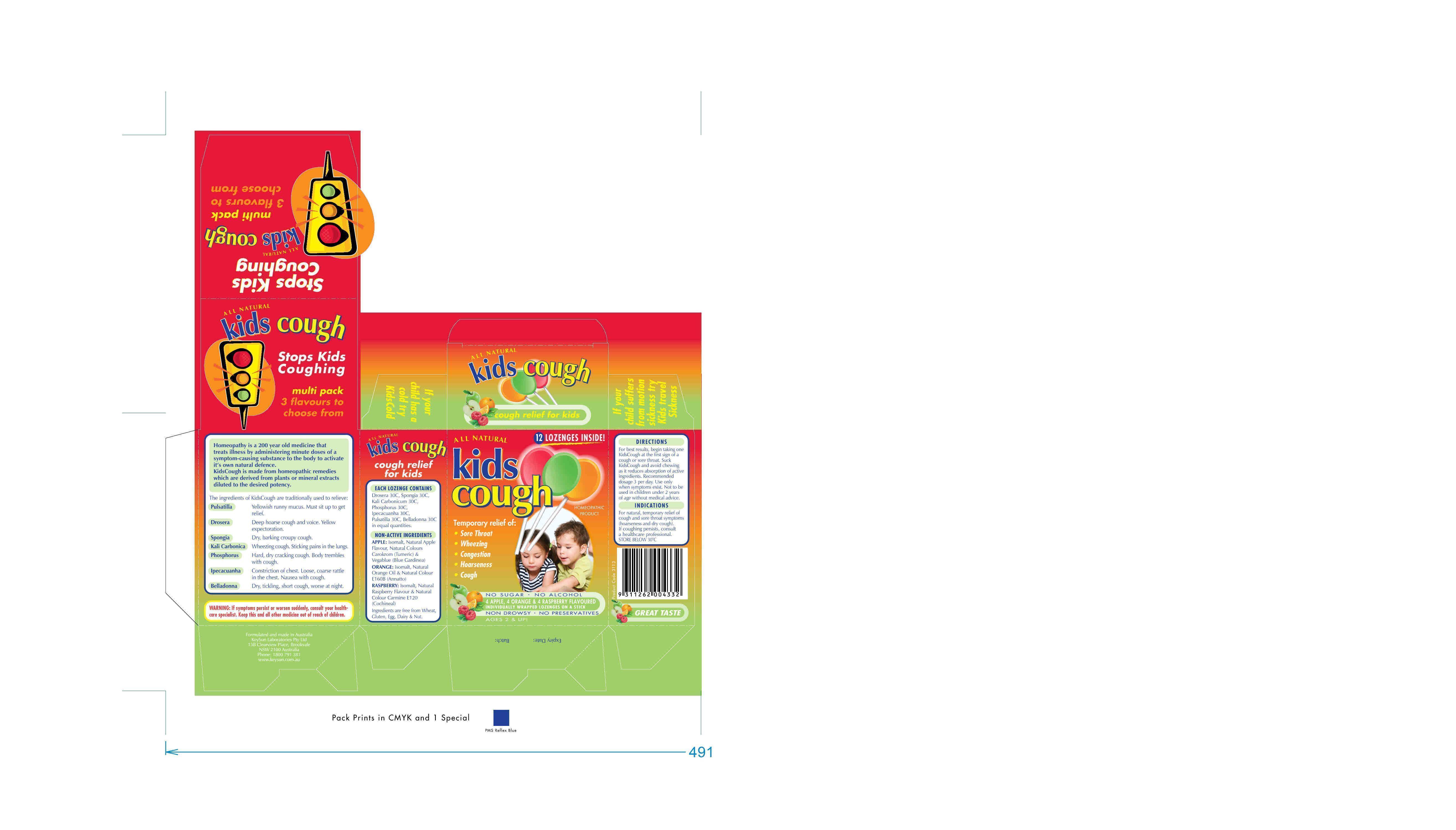 DRUG LABEL: kids cough
                
                
NDC: 76509-800 | Form: KIT | Route: ORAL
Manufacturer: Natures Investment Holdings Pty Ltd dba Maxrelief USA
Category: homeopathic | Type: HUMAN OTC DRUG LABEL
Date: 20140529

ACTIVE INGREDIENTS: DROSERA INTERMEDIA 30 [hp_X]/1 1; SPONGIA OFFICINALIS WHOLE 30 [hp_X]/1 1; POTASSIUM CARBONATE 30 [hp_X]/1 1; PHOSPHORUS 30 [hp_X]/1 1; PULSATILLA VULGARIS 30 [hp_X]/1 1; ATROPA BELLADONNA 30 [hp_X]/1 1; IPECAC 30 [hp_X]/1 1; DROSERA INTERMEDIA 30 [hp_X]/1 1; SPONGIA OFFICINALIS WHOLE 30 [hp_X]/1 1; POTASSIUM CARBONATE 30 [hp_X]/1 1; PHOSPHORUS 30 [hp_X]/1 1; PULSATILLA VULGARIS 30 [hp_X]/1 1; ATROPA BELLADONNA 30 [hp_X]/1 1; IPECAC 30 [hp_X]/1 1; DROSERA INTERMEDIA 30 [hp_X]/1 1; SPONGIA OFFICINALIS WHOLE 30 [hp_X]/1 1; POTASSIUM CARBONATE 30 [hp_X]/1 1; PHOSPHORUS 30 [hp_X]/1 1; PULSATILLA VULGARIS 30 [hp_X]/1 1; ATROPA BELLADONNA 30 [hp_X]/1 1; IPECAC 30 [hp_X]/1 1
INACTIVE INGREDIENTS: ISOMALT; ISOMALT; ISOMALT; COCHINEAL

Drug Facts

INACTIVE INGREDIENT

Non-Active Ingredients

Non-active ingredients for kids cough apple:

Isomalt, Natural Apple Flavour, Natural

Colours, Carokram and Vegetable (Blue Gardinea)

Non-active ingredients for kids cough orange:

Isomalt, Natural Orange and Colour (Annato),

Non-active ingredients for kids cough raspberry:

Isomalt, Natural Raspberry Flavour and Natural

Colour Carmine (Cochineal)

Active Ingredients for kids cough apple:

Each lozenge contains:

Drosera 30C, Spongia 30C, Kali Carbonicum 30C,

Phospherous 30C, Ipercacuanha 30C, Pulsatilla 30C,

Belladonna 30C

in equal quantities.

Active Ingredients for kids cough orange:

Each lozenge contains:

Drosera 30C, Spongia 30C, Kali Carbonicum 30C,

Phospherous 30C, Ipercacuanha 30C, Pulsatilla 30C,

Belladonna 30C

in equal quantities.

Active Ingredients for kids cough raspberry:

Each lozenge contains:

Drosera 30C, Spongia 30C, Kali Carbonicum 30C,

Phospherous 30C, Ipercacuanha 30C, Pulsatilla 30C,

Belladonna 30C

in equal quantities

PURPOSE

Indications

Indications for kids cough apple:

For natural, temporary relief of cough and

sore throat symptoms (hoarseness and dry cough).

Indications for kids cough orange:

For natural, temporary relief of cough and

sore throat symptoms (hoarseness and dry cough).

Indications for kids cough raspberry:

For natural, temporary relief of cough and

sore throat symptoms (hoarseness and dry cough).

Warning:

Warning for kids cough apple:

If symptoms persist or suddenly worsen, consult your

healthcare specialist.

Warning for kids cough orange:

If symptoms persist or suddenly worsen, consult your

healthcare specialist.

Warning for kids cough raspberry:

If symptoms persist or suddenly worsen, consult your

healthcare specialist.

Keep Out of Reach of Children for kids cough apple:

Keep this and all other medicine out of reach of children.

Keep Out of Reach of Children for kids cough orange:

Keep this and all other medicine out of reach of children.

Keep Out of Reach of Children for kids cough raspberry:

Keep this and all other medicine out of reach of children.

Directions

Directions for kids cough apple:

For best results, begin taking one

KIdsCough at the first sign of a cough or sore throat.

Suck KidsCough and avoid chewing as it reduces

absorption of active ingredients. Recommended dosage 3 per day.

Use only when symptoms exist. Not to be used

in children under 2 years of age without medical advice.

Directions for kids cough orange:

For best results, begin taking one

KidsCough at the first sign of a cough or sore throat.

Suck KidsCough and avoid chewing as it reduces

absorption of active ingredients. Recommended dosage 3 per day.

Use only when symptoms exist. Not to be used

in children under 2 years of age without medical advice.

Directions for kids cough raspberry:

For best results, begin taking one

KidsCough at the first sign of a cough or sore throat.

Suck KidsCough and avoid chewing as it reduces

absorption of active ingredients. Recommended dosage 3 per day.

Use only when symptoms exist. Not to be used

in children under 2 years of age without medical advice.

Indications for kids cough apple:

For natural, temporary relief of cough

and sore throat symptoms (hoarseness and

dry cough). If coughing persists,

consult a heathcare professional.

Indications for kids cough orange:

For natural, temporary relief of cough

and sore throat symptoms (hoarseness and

dry cough). If coughing persists,

consult a healthcare professional.

Indications for kids cough raspberry:

For natural, temporary relief of cough

and sore throat symptoms (hoarseness and

dry cough). If coughing persists, consult a

healthcare professional.

Storage and Handling for kids cough apple:

STORE BELOW 30 C

Storage and Handling for kids cough orange:

STORE BELOW 30 C

Storage and Handling for kids cough raspberry:

STORE BELOW 30 C